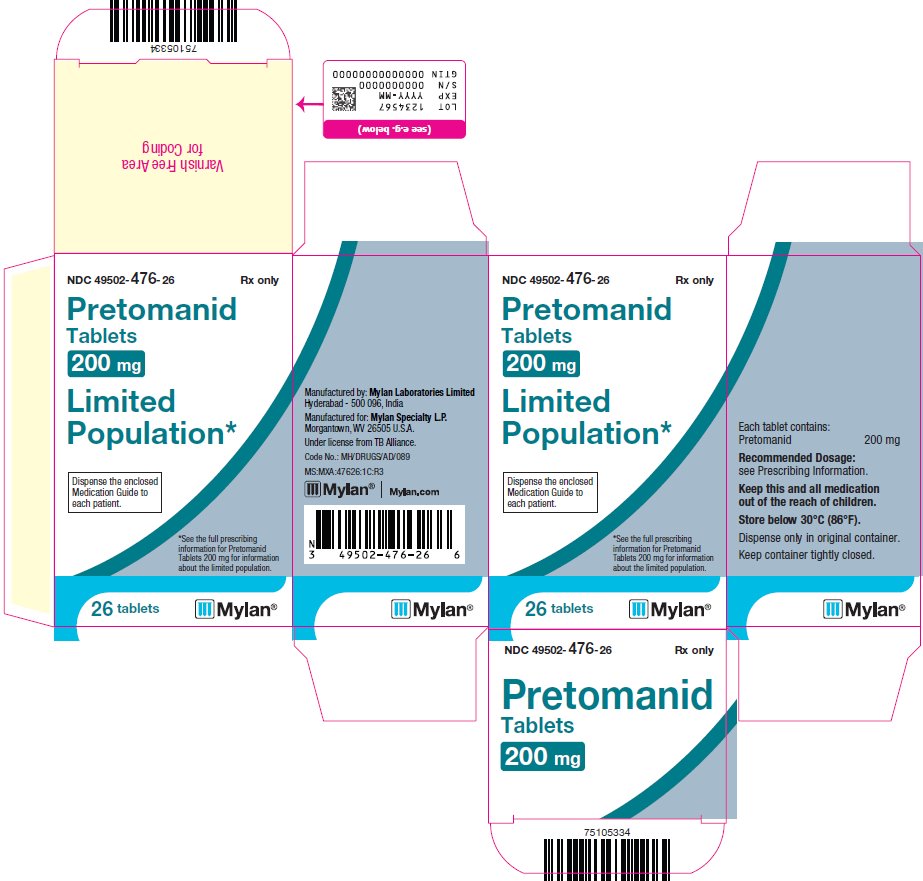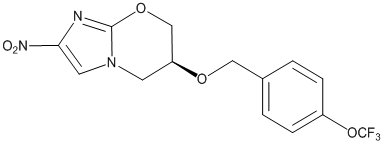 DRUG LABEL: Pretomanid
NDC: 49502-476 | Form: TABLET
Manufacturer: Viatris Specialty LLC
Category: prescription | Type: HUMAN PRESCRIPTION DRUG LABEL
Date: 20241115

ACTIVE INGREDIENTS: Pretomanid 200 mg/1 1
INACTIVE INGREDIENTS: SILICON DIOXIDE; LACTOSE MONOHYDRATE; MAGNESIUM STEARATE; MICROCRYSTALLINE CELLULOSE; POVIDONE, UNSPECIFIED; SODIUM LAURYL SULFATE; SODIUM STARCH GLYCOLATE TYPE A

HIGHLIGHTS OF PRESCRIBING INFORMATION

These highlights do not include all the information needed to use PRETOMANID TABLETS safely and effectively. See full prescribing information for PRETOMANID TABLETS.
PRETOMANID tablets, for oral use
Initial U.S. Approval: 2019
LIMITED POPULATION

RECENT MAJOR CHANGES

Dosage and Administration (2.1, 2.2) 11/2024

Warnings and Precautions (5.3, 5.4) 11/2024

1 INDICATIONS AND USAGE

Limited Population: Pretomanid Tablet is an antimycobacterial indicated, as part of a combination regimen with bedaquiline and linezolid for the treatment of adults with pulmonary tuberculosis (TB) that is resistant to isoniazid, rifamycins, a fluoroquinolone and a second line injectable antibacterial drug OR adults with pulmonary TB resistant to isoniazid and rifampin, who are treatment-intolerant or nonresponsive to standard therapy. Approval of this indication is based on limited clinical safety and efficacy data. This drug is indicated for use in a limited and specific population of patients. (1)

Limitations of Use: (1)

Pretomanid Tablets are not indicated in patients with:

- Drug-sensitive (DS) TB
- Latent infection due to Mycobacterium tuberculosis
- Extra-pulmonary infection due to Mycobacterium tuberculosis
- TB resistant to isoniazid and rifampin, who are responsive to standard therapy and not treatment-intolerant
- TB with known resistance to any component of the combination

Safety and effectiveness of Pretomanid Tablets have not been established for its use in combination with drugs other than bedaquiline and linezolid as part of the recommended dosing regimen.

2 DOSAGE AND ADMINISTRATION

Important Administration Instructions: (2.1)

- Pretomanid Tablets must be administered only in combination with bedaquiline and linezolid as part of the recommended dosage regimen.
- Administer the combination regimen of Pretomanid Tablets, bedaquiline, and linezolid by directly observed therapy (DOT).
- Pretomanid Tablets must be administered in combination with bedaquiline and linezolid with food.
- Doses of the combination regimen missed for safety reasons can be made up at the end of treatment; doses of linezolid alone missed due to linezolid adverse reactions should not be made up.
- Administer Pretomanid Tablets in combination with bedaquiline and linezolid as follows: (2.2)
- Pretomanid Tablets:
  - Pretomanid Tablet 200 mg orally once daily for 26 weeks. Administer Pretomanid Tablets whole with water.
  - For patients with swallowing difficulties see the full prescribing information for crushing or soaking followed by crushing instructions of the Pretomanid Tablets.
- Bedaquiline:
  - Bedaquiline 400 mg orally once daily for 2 weeks followed by 200 mg 3 times per week, with at least 48 hours between doses, for 24 weeks for a total of 26 weeks.
  - Bedaquiline 200 mg orally once daily for 8 weeks followed by 100 mg once daily for 18 weeks, for a total of 26 weeks.
- Linezolid:
  - Linezolid Preferred: 600 mg orally once daily for 26 weeks. Alternative: 1,200 mg orally once daily for 26 weeks.
  - If myelosuppression, peripheral neuropathy, or optic neuropathy occurs, reduce or interrupt linezolid dosing as necessary.

3 DOSAGE FORMS AND STRENGTHS

Tablets: 200 mg (3)

4 CONTRAINDICATIONS

- Pretomanid Tablets used in combination with bedaquiline and linezolid are contraindicated in patients for whom bedaquiline and/or linezolid is contraindicated. (4)

5 WARNINGS AND PRECAUTIONS

- Hepatic adverse reactions were reported with the use of the combination regimen of Pretomanid Tablets, bedaquiline, and linezolid. Monitor symptoms and signs and liver‑related laboratory tests. Interrupt treatment with the entire regimen if evidence of liver injury occurs. (5.2)
- Myelosuppression was reported with the use of the combination regimen of Pretomanid Tablets, bedaquiline, and linezolid. Monitor complete blood counts. Decrease or interrupt linezolid dosing if significant myelosuppression develops or worsens. (5.3)
- Peripheral and optic neuropathy were reported with the use of the combination regimen of Pretomanid Tablets, bedaquiline, and linezolid. Monitor visual function. Obtain an ophthalmologic evaluation if there are symptoms of visual impairment. Decrease or interrupt linezolid dosing if neuropathy develops or worsens. (5.4)
- QT prolongation was reported with the use of the combination regimen of Pretomanid Tablets, bedaquiline, and linezolid. Use with drugs that prolong the QT interval may cause additive QT prolongation. Monitor ECGs. Discontinue the combination regimen of Pretomanid Tablets, bedaquiline, and linezolid if significant ventricular arrhythmia or if QTcF interval prolongation of greater than 500 ms develops. (5.5)
- Reproductive effects: Pretomanid caused testicular atrophy and impaired fertility in male rats. Advise patients of reproductive toxicities seen in animal studies and that the potential effects on human male fertility have not been adequately evaluated. (5.7, 13.1)
- Lactic acidosis was reported with the use of the combination regimen of Pretomanid Tablets, bedaquiline, and linezolid. Consider interrupting linezolid or the entire combination regimen of Pretomanid Tablets, bedaquiline, and linezolid dosing if significant lactic acidosis develops. (5.8)

6 ADVERSE REACTIONS

Most common adverse reactions (≥ 10%) are peripheral neuropathy, anemia, nausea, acne, vomiting, increased transaminases, headache, musculoskeletal pain, dyspepsia, rash, pruritus, decreased appetite, abdominal pain, pleuritic pain, increased gamma-glutamyltransferase, hemoptysis and hyperamylasemia. (6)

To report SUSPECTED ADVERSE REACTIONS, contact Mylan at 1-877-446-3679 (1-877-4-INFO-RX) or FDA at 1-800-FDA-1088 or www.fda.gov/medwatch.

7 DRUG INTERACTIONS

- Strong or moderate CYP3A4 inducers such as rifampin or efavirenz: Avoid co-administration. (5.6, 7.1)
- Organic anion transporter-3 (OAT3) substrates: Monitor for OAT3 substrate drug-related adverse reactions and consider dosage reduction for OAT3 substrate drugs, if needed. (7.2)

8 USE IN SPECIFIC POPULATIONS

- Lactation: Breastfeeding is not recommended. (8.2)

FULL PRESCRIBING INFORMATION

1 INDICATIONS AND USAGE

Limited Population: Pretomanid Tablet is indicated, as part of a combination regimen with bedaquiline and linezolid for the treatment of adults with pulmonary tuberculosis (TB) resistant to isoniazid, rifamycins, a fluoroquinolone and a second line injectable antibacterial drug OR adults with pulmonary TB resistant to isoniazid and rifampin, who are treatment-intolerant or nonresponsive to standard therapy. Approval of this indication is based on limited clinical safety and efficacy data. This drug is indicated for use in a limited and specific population of patients.

Limitations of Use:

- Pretomanid Tablets are not indicated in patients with:
  - Drug-sensitive (DS) TB
  - Latent infection due to Mycobacterium tuberculosis
  - Extra-pulmonary infection due to Mycobacterium tuberculosis
  - TB resistant to isoniazid and rifampin who are responsive to standard therapy and not treatment-intolerant
  - TB with known resistance to any component of the combination
- Safety and effectiveness of Pretomanid Tablets have not been established for its use in combination with drugs other than bedaquiline and linezolid as part of the recommended dosing regimen [see Dosage and Administration (2.2)].

2 DOSAGE AND ADMINISTRATION

2.1 Important Administration Instructions

- Pretomanid Tablets must be administered only in combination with bedaquiline and linezolid as part of the recommended dosage regimen [see Dosage and Administration (2.2)].
- Administer the combination regimen of Pretomanid Tablets, bedaquiline, and linezolid by directly observed therapy (DOT).
- Pretomanid Tablets must be administered in combination with bedaquiline and linezolid with food [see Clinical Pharmacology (12.3)].
- Emphasize the need for compliance with the full course of therapy to patients [see Patient Counseling Information (17)].
- If the combination regimen of Pretomanid Tablets, bedaquiline, and linezolid is interrupted by a healthcare provider for safety reasons, missed doses can be made up at the end of the treatment; doses of linezolid alone missed due to linezolid adverse reactions should not be made up [see Dosage and Administration (2.4)].
- Dosing of the combination regimen of Pretomanid Tablets, bedaquiline, and linezolid can be extended beyond 26 weeks, if necessary [see Clinical Studies (14)].

2.2 Recommended Dosage

Pretomanid Tablets must be administered in combination with bedaquiline and linezolid with food [see Clinical Pharmacology (12.3)]. The recommended dosage and duration for Pretomanid Tablets, bedaquiline and linezolid when administered in the combination regimen are as follows:

Pretomanid Tablets:

- Administer Pretomanid Tablet 200 mg orally (1 tablet of 200 mg), once daily, for 26 weeks with food.
- Administer Pretomanid Tablets whole with water.
- For adult patients with swallowing difficulties, use one of the following two methods:
A) Crush and Suspend Pretomanid Tablets
- Crush and suspend Pretomanid Tablet in one teaspoon (approximately 5 mL) of room temperature water in a drinking cup and mix well by vigorous stirring.
- Orally administer the contents of the cup immediately.
- To ensure no tablet residual is left in the cup, rinse with an additional one teaspoon (approximately 5 mL) of water and orally administer the contents of the cup immediately.
- Do not store the mixture for later use.
B) Soak and then Crush Pretomanid Tablets
- Soak Pretomanid Tablet for 4 to 5 minutes in one teaspoon (approximately 5 mL) of room temperature water in a drinking cup and then any remaining solid should be crushed. Mix the contents of the cup well by vigorous stirring.
- Orally administer the contents of the cup immediately.
- To ensure no tablet residual is left in the cup, rinse with an additional one teaspoon (approximately 5 mL) of water and orally administer the contents of the cup immediately.
- Do not store the mixture for later use.

Bedaquiline:

Use one of the following two dosage regimens of bedaquiline:

- Bedaquiline 400 mg orally once daily for 2 weeks followed by 200 mg 3 times per week, with at least 48 hours between doses, for 24 weeks, for a total of 26 weeks.
- Bedaquiline 200 mg orally once daily for 8 weeks followed by 100 mg once daily for 18 weeks, for a total of 26 weeks.

Linezolid:

- Preferred linezolid dosage regimen: 600 mg orally once daily for 26 weeks. If myelosuppression, peripheral neuropathy, or optic neuropathy occurs, reduce linezolid dosage to 300 mg once daily or interrupt linezolid dosing [see Dosage and Administration (2.4), Warnings and Precautions (5.3, 5.4), and Adverse Reactions (6.1)].
- Alternative linezolid dosage regimen: 1,200 mg orally once daily for 26 weeks. If myelosuppression, peripheral neuropathy, or optic neuropathy occurs, reduce linezolid dosage to 600 mg once daily, further reduce linezolid dosage to 300 mg once daily, or interrupt linezolid dosing [see Dosage and Administration (2.4), Warnings and Precautions (5.3, 5.4), and Adverse Reactions (6.1)].

2.3 Assessments Prior to Initiating the Combination Regimen of Pretomanid Tablets, Bedaquiline, and Linezolid

- Assess for symptoms and signs of liver disease (such as fatigue, anorexia, nausea, jaundice, dark urine, liver tenderness, and hepatomegaly). Obtain laboratory tests (alanine aminotransferase [ALT], aspartate aminotransferase [AST], alkaline phosphatase, and bilirubin) [see Warnings and Precautions (5.2)].
- Obtain complete blood count [see Warnings and Precautions (5.3)]. Obtain serum potassium, calcium, and magnesium and correct if abnormal [see Warnings and Precautions (5.5)]. Obtain an ECG before initiation of treatment [see Warnings and Precautions (5.5)].

2.4 Discontinuation of Dosing

If either bedaquiline or Pretomanid Tablets are discontinued, the entire combination regimen should also be discontinued.

If linezolid is permanently discontinued during the initial four consecutive weeks of treatment, bedaquiline and Pretomanid Tablets should also be discontinued. If linezolid is discontinued after the initial four weeks of consecutive treatment, continue administering bedaquiline and Pretomanid Tablets [see Dosage and Administration (2.2)].

3 DOSAGE FORMS AND STRENGTHS

Pretomanid Tablets, 200 mg, are white to off-white, oval tablets debossed with M on one side and P200 on the other side.

4 CONTRAINDICATIONS

Pretomanid Tablets used in the combination regimen with bedaquiline and linezolid are contraindicated in patients for whom bedaquiline and/or linezolid are contraindicated. Refer to the bedaquiline and linezolid prescribing information.

5 WARNINGS AND PRECAUTIONS

5.1 Risks Associated with the Combination Treatment Regimen

Pretomanid Tablet is indicated for use as part of a regimen in combination with bedaquiline and linezolid. Refer to the prescribing information for bedaquiline and linezolid for additional risk information. Warnings and Precautions related to bedaquiline and linezolid also apply to their use in the combination regimen with Pretomanid Tablets.

5.2 Hepatotoxicity

Hepatic adverse reactions were reported with the combination regimen of Pretomanid Tablets, bedaquiline, and linezolid [see Warnings and Precautions (5.1), and Adverse Reactions (6.1)]. Avoid alcohol and hepatotoxic agents, including herbal supplements and drugs other than bedaquiline and linezolid [see Indications and Usage (1)] while on Pretomanid Tablets, especially in patients with impaired hepatic function.

Monitor symptoms and signs (such as fatigue, anorexia, nausea, jaundice, dark urine, liver tenderness, and hepatomegaly) and laboratory tests (ALT, AST, alkaline phosphatase, and bilirubin) at a minimum at baseline, at two weeks, and then monthly while on treatment and as needed. If evidence of new or worsening liver dysfunction occurs, test for viral hepatitides and discontinue other hepatotoxic medications. Interrupt treatment with the entire regimen if:

- Aminotransferase elevations are accompanied by total bilirubin elevation greater than 2 times the upper limit of normal.
- Aminotransferase elevations are greater than 8 times the upper limit of normal.
- Aminotransferase elevations are greater than 5 times the upper limit of normal and persist beyond 2 weeks.

5.3 Myelosuppression

Myelosuppression (including anemia, leukopenia, thrombocytopenia, and pancytopenia) was reported with the combination regimen of Pretomanid Tablets, bedaquiline, and linezolid. Myelosuppression is a known adverse reaction of linezolid. Anemia can be life threatening [see Warnings and Precautions (5.1), and Adverse Reactions (6.1)]. When linezolid dosing, as part of the combination regimen of Pretomanid Tablets, bedaquiline, and linezolid, was reduced, interrupted, or discontinued, the observed hematologic abnormalities were reversible. Complete blood counts should be monitored at a minimum at baseline, at two weeks, and then monthly in patients receiving linezolid as part of the combination regimen of Pretomanid Tablets, bedaquiline, and linezolid. Decreasing linezolid to half the initial dose or interrupting linezolid dosing should be considered in patients who develop or have worsening myelosuppression [see Dosage and Administration (2.2)].

5.4 Peripheral and Optic Neuropathy

Peripheral neuropathy and optic neuropathy were reported with the combination regimen of Pretomanid Tablets, bedaquiline, and linezolid [see Warnings and Precautions (5.1), and Adverse Reactions (6.1)]. Neuropathy is a known adverse reaction of long-term linezolid use. Neuropathy associated with linezolid is generally reversible or improved with appropriate monitoring and interruption, dose reduction, or discontinuation of linezolid dosing. When improvement in the peripheral neuropathy is observed, consider resuming linezolid at half the initial dose [see Dosage and Administration (2.2)]. Monitor visual function in all patients receiving the combination regimen of Pretomanid Tablets, bedaquiline, and linezolid; if a patient experiences symptoms of visual impairment, interrupt linezolid dosing and obtain prompt ophthalmologic evaluation.

5.5 QT Prolongation

QT prolongation was reported with the combination regimen of Pretomanid Tablets, bedaquiline, and linezolid [see Warnings and Precautions (5.1), Adverse Reactions (6.1), and Clinical Pharmacology (12.2)]. QT prolongation is a known adverse reaction of bedaquiline. Obtain an ECG before initiation of treatment, and at least 2, 12, and 24 weeks after starting treatment with the combination regimen of Pretomanid Tablets, bedaquiline, and linezolid. Obtain serum potassium, calcium, and magnesium at baseline and correct if abnormal. Monitor these electrolytes if QT prolongation is detected [see Adverse Reactions (6.1)].

The following may increase the risk for QT prolongation when patients are receiving bedaquiline as part of the combination regimen of Pretomanid Tablets, bedaquiline, and linezolid: a history of Torsade de Pointes, congenital long QT syndrome, ongoing hypothyroidism, ongoing bradyarrhythmia, uncompensated heart failure, or serum calcium, magnesium, or potassium levels below the lower limits of normal. If necessary, bedaquiline treatment initiation could be considered in these patients after a favorable benefit-risk assessment and with frequent ECG monitoring.

Discontinue the combination regimen of Pretomanid Tablets, bedaquiline, and linezolid if the patient develops clinically significant ventricular arrhythmia or a QTcF interval of greater than 500 ms (confirmed by repeat ECG). If syncope occurs, obtain an ECG to detect QT prolongation.

5.6 Drug Interactions

CYP3A4 Inducers

Pretomanid may be in part metabolized by CYP3A4 [see Drug Interactions (7.1) and Clinical Pharmacology (12.3)]. Avoid co‑administration of strong or moderate CYP3A4 inducers, such as rifampin or efavirenz, during treatment with pretomanid.

5.7 Reproductive Effects

Pretomanid caused testicular atrophy and impaired fertility in male rats. Advise patients of reproductive toxicities seen in animal studies and that the potential effects on human male fertility have not been adequately evaluated [see Use in Specific Populations (8.3) and Nonclinical Toxicology (13.1)].

5.8 Lactic Acidosis

Lactic acidosis was reported with the combination regimen of Pretomanid Tablets, bedaquiline, and linezolid [see Warnings and Precautions (5.1) and Adverse Reactions (6.1)]. Lactic acidosis is a known adverse reaction of linezolid. Patients who develop recurrent nausea or vomiting should receive immediate medical evaluation, including evaluation of bicarbonate and lactic acid levels, and interruption of linezolid or the entire combination regimen of Pretomanid Tablets, bedaquiline, and linezolid should be considered.

6 ADVERSE REACTIONS

The following serious adverse reactions are discussed here and elsewhere in the labeling:

- Hepatotoxicity [see Warnings and Precautions (5.2)]
- Myelosuppression [see Warnings and Precautions (5.3)]
- Peripheral and Optic Neuropathy [see Warnings and Precautions (5.4)]
- QT Prolongation [see Warnings and Precautions (5.5)]
- Reproductive Effects [see Warnings and Precautions (5.7)]
- Lactic Acidosis [see Warnings and Precautions (5.8)]

6.1 Clinical Trials Experience

Because clinical studies are conducted under widely varying conditions, adverse reaction rates observed in the clinical studies of a drug cannot be directly compared to the rates in the clinical studies of another drug and may not reflect the rates observed in clinical practice.

When Pretomanid Tablets are administered in combination with bedaquiline and linezolid, refer to the prescribing information for the respective drugs for a description of the adverse reactions associated with their use.

Approximately 3100 subjects have been exposed to Pretomanid Tablets, either alone or as part of a combination therapy in clinical trials.

The registrational trial, Trial 1 (NCT02333799), was a single-arm, open-label trial conducted in three sites in South Africa in which adult patients with pulmonary TB resistant to isoniazid, rifamycins, a fluoroquinolone and a second line injectable antibacterial drug or pulmonary TB resistant to isoniazid and rifampin, who were treatment-intolerant or non-responsive to standard therapy received the combination regimen of Pretomanid Tablets, bedaquiline, and linezolid for 6 months (extendable to 9 months) with 24 months of follow-up. One hundred and nine patients were treated; 76% were black, and 23% were of mixed race. Their ages ranged from 17 years to 60 years (mean 36 years), and all patients were from South Africa. Fifty-six (51%) patients were HIV-positive. There were 8 deaths. Six patients died while receiving treatment; all surviving patients, excluding one patient who withdrew consent, completed treatment. Two patients died during follow-up at Day 369 and Day 486, respectively.

Trial 2 (NCT03086486) was a phase 3 partially-blinded, randomized trial assessing the safety and efficacy of various doses and treatment durations of linezolid in combination with Pretomanid Tablets plus bedaquiline in patients with pulmonary TB resistant to isoniazid, rifamycins, a fluoroquinolone and a second line injectable antibacterial drug, or pulmonary TB resistant to rifamycins and either a fluoroquinolone or a second line injectable antibacterial drug, or pulmonary TB resistant to isoniazid and rifampin who were treatment intolerant or non-responsive to standard therapy.

A total of 181 patients were randomized to one of the 4 treatment arms, Pretomanid Tablets plus bedaquiline plus either 1,200 mg or 600 mg of linezolid for 26 weeks or for 9 weeks (not an approved dosing regimen), followed by a linezolid placebo for 17 weeks. Males represented 67% of the patients in the trial and the median age of all patients was 36 years. 64% of patients were White and the remaining patients were Black (36%). The treatment groups were comparable with respect to demographic characteristics. Most patients (93%) completed treatment. One patient died in the linezolid 1,200 mg for 9 weeks (not an approved dosing regimen) arm.

Common Adverse Reactions Reported in Trials 1 and 2

Table 1 summarizes the incidence of select adverse reactions occurring in ≥ 5% of patients treated for 26 weeks in Trials 1 and 2.

Table 1: Select Adverse Reactions (All Grades) Reported in ≥ 5% of Patients Receiving the Combination Regimen of Pretomanid Tablets, Bedaquiline, and Linezolid in Trials 1 and 2
 | Pretomanid Tablets, Bedaquiline and Linezolid (1,200 mg) Combination Regimen (N = 154) | Pretomanid Tablets, Bedaquiline and Linezolid (600 mg) Combination Regimen (N = 45)
Adverse Reactions | All Grades n (%) | All Grades n (%)
Peripheral neuropathy [Select terms are collapsed, as follows: peripheral neuropathy (burning sensation, hypoesthesia, hyporeflexia, neuropathy peripheral, paresthesia, peripheral motor neuropathy, peripheral sensorimotor neuropathy, peripheral sensory neuropathy, polyneuropathy, sensory disturbance); anemia (anemia); acne (acne, dermatitis acneiform); transaminases increased (alanine aminotransferase [ALT]) increased, aspartate aminotransferase [AST] increased, drug-induced liver injury, hepatic enzyme increased, hepatic function abnormal, liver function test increased, transaminases increased); musculoskeletal pain (arthralgia, back pain, costochondritis, myalgia, pain in extremity); rash (rash, rash erythematous, rash maculo-papular, rash papular, rash vesicular); pruritus (pruritus, pruritus generalized, rash pruritic); abdominal pain (abdominal pain, abdominal pain lower, abdominal pain upper, abdominal tenderness); hyperamylasemia (amylase increased, hyperamylasemia); hypertension (blood pressure increased, hypertension); cough (cough, productive cough); visual impairment (vision blurred, visual acuity reduced, visual impairment); neutropenia (neutropenia); hyperlipasemia (hyperlipasemia, lipase increased).] | 105 (68) | 10 (22)
Anemia | 48 (31)
Nausea | 46 (30)
Acne | 44 (29) | 6 (13)
Vomiting | 40 (26)
Transaminases increased | 39 (25) | 11 (24)
Headache | 34 (22)
Musculoskeletal pain | 34 (22)
Dyspepsia | 30 (19)
Rash | 29 (19)
Pruritus | 25 (16) | 3 (7)
Decreased appetite | 24 (16)
Abdominal pain | 22 (14)
Pleuritic pain | 22 (14) | 4 (9)
Gamma-glutamyltransferase increased | 20 (13)
Hemoptysis | 17 (11)
Hyperamylasemia | 15 (10)
Diarrhea | 14 (9)
Hypertension | 14 (9)
Cough | 13 (8)
Visual impairment | 13 (8)
Hypoglycemia | 12 (8)
Neutropenia | 12 (8) | 3 (7)
Abnormal loss of weight | 11 (7)
Constipation | 9 (6)
Gastritis | 9 (6)
Hyperlipasemia | 9 (6)
Insomnia | 9 (6)
Dry skin | 8 (5)

The following select adverse reactions were reported in patients receiving the combination regimen of Pretomanid Tablets, bedaquiline and linezolid (1,200 mg) at a rate of less than 5% in Trials 1 and 2:

Gastrointestinal Disorders: pancreatitis, dysgeusia

Investigations: blood creatine phosphokinase increase, blood creatinine increase, blood alkaline phosphatase increase

Blood and Lymphatic System Disorders: leukopenia, thrombocytopenia

Metabolism and Nutrition Disorders: hypomagnesemia, hyperglycemia, hypokalemia, hyperkalemia, hyponatremia

Nervous System Disorders: dizziness, seizure

The following select adverse reactions were reported in patients receiving the combination regimen of Pretomanid Tablets, bedaquiline and linezolid (600 mg) at a rate of less than 5% in Trial 2:

Blood and Lymphatic System Disorders: anemia, thrombocytopenia

Metabolism and Nutrition Disorders: decreased appetite, hyperlipasemia, hypoglycemia, hypophosphatemia, hypomagnesemia, hyperkalemia

Psychiatric Disorders: insomnia

Nervous System Disorders: headache

Vascular Disorders: hypertension

Respiratory, Thoracic and Mediastinal Disorders: cough, hemoptysis

Gastrointestinal Disorders: abdominal pain, constipation, diarrhea, dyspepsia, nausea, vomiting

Skin and Subcutaneous Tissue Disorders: dry skin, rash

Musculoskeletal and Connective Tissue Disorders: musculoskeletal pain

Laboratory Abnormalities Reported in Trials 1 and 2

Table 2 summarizes select laboratory abnormalities in patients treated for 26 weeks in Trials 1 and 2.

Table 2: Select Laboratory Abnormalities in Clinical Trials
Parameter; Multiples of Upper Limit of Normal (x ULN) | Combination Regimen of Pretomanid Tablets, Bedaquiline, and Linezolid (1,200 mg) (N = 154) n (%) | Combination Regimen of Pretomanid Tablets, Bedaquiline, and Linezolid (600 mg) (N = 45) n (%)
Transaminases and Bilirubin
Alanine Aminotransferase (ALT)
> 3 and ≤ 5 X ULN | 13 (8) | 3 (7)
> 5 and ≤ 8 X ULN | 6 (4) | 0 (0)
> 8 X ULN | 1 (1) | 1 (2)
Aspartate Aminotransferase (AST)
> 3 and ≤ 5 X ULN | 7 (5) | 0 (0)
> 5 and ≤ 8 X ULN | 3 (2) | 0 (0)
> 8 X ULN | 1 (1) | 1 (2)
Total Bilirubin
> 1 X ULN and ≤ 2 X ULN | 8 (5) | 1 (2)
> 2 X ULN | 2 (1) | 1 (2)
Hematology
Hemoglobin
≤ 7.9 g/dL | 6 (4) | 0 (0)
Neutrophils Absolute Count
≤ 749/mm^3 | 6 (4) | 1 (2)
Platelets
≤ 49,999/mm^3 | 2 (1) | 0 (0)
Serum Chemistry
Lipase
> 2 X ULN | 7 (5) | 2 (4)
ULN = upper limit of normal

In Trial 1, 28% of patients experienced increased transaminases. Except for one patient who died due to pneumonia and sepsis, all patients who experienced increased transaminases were able to continue therapy and complete the full course of treatment. In Trial 2, 47 of 181 patients (26%) had one or more liver-related adverse reactions, with similar numbers in each group.

Myelosuppression is a known adverse reaction of linezolid. In Trial 1, the most common hematopoietic cytopenia was anemia (37%). The majority of cytopenias began after 2 weeks of treatment. Three patients experienced cytopenias that were considered serious: neutropenia in 1 patient and anemia in 2 patients. All 3 serious adverse reactions resulted in interruption of linezolid or all components of the combination regimen of Pretomanid Tablets, bedaquiline, and linezolid, and all resolved.

In Trial 2, there was a greater incidence of myelosuppression, 29% versus 13%, for the 1,200 mg compared to the 600 mg linezolid 26-week group. Most of the myelosuppression-related adverse reactions were either grade 1 or grade 2 in severity.

In the combined study data for Trial 1 and Trial 2, 2 patients reported serious adverse reactions of anemia with linezolid 1,200 mg, and none were reported in the 600 mg group.

Peripheral and Optic Neuropathy

Peripheral neuropathy is a known adverse reaction of linezolid. In Trial 1, peripheral neuropathy was reported in 81% of patients. Most of these adverse reactions (64%) occurred after 8 weeks of treatment and resulted in dosing interruption, dose reduction, or discontinuation of linezolid. Severe, moderate, and mild peripheral neuropathy occurred in 22%, 32%, and 26% of patients, respectively. No adverse reaction related to peripheral neuropathy led to a discontinuation of the entire study regimen.

In Trial 2, 17 (38%) patients reported an adverse reaction of peripheral neuropathy in the 1,200 mg 26-week treatment group; one of these reactions led to treatment discontinuation. In the 600 mg 26-week treatment group, 10 (22%) patients reported peripheral neuropathy, and none required linezolid treatment interruption or treatment discontinuation.

Optic neuropathy is a known adverse reaction of linezolid. Two patients (2%) in Trial 1 developed optic neuropathy after 16 weeks of treatment. Both were serious, confirmed on retinal examination as optic neuropathy/neuritis, and resulted in discontinuation of linezolid; both adverse reactions resolved.

Overall, patients administered a linezolid dose of 600 mg twice daily had a similar safety profile to those administered a dose of 1,200 mg once daily.

In Trial 2 overall, 4 (2%) patients reported an adverse reaction of optic neuropathy. All 4 patients were in the 1,200 mg linezolid 26-week treatment group (9%). The maximum severity was grade 1 (mild) for 1 patient, grade 2 (moderate) for 2 patients, and grade 3 (severe) for 1 patient. All patients had linezolid permanently discontinued except 1 patient who had already completed treatment when the adverse reaction occurred. Onset of optic neuropathy occurred after 3 months of treatment, and resolved.

7 DRUG INTERACTIONS

7.1 Effect of Other Drugs on Pretomanid

CYP3A4 Inducers

Co-administration of pretomanid with rifampin and efavirenz resulted in a decrease in pretomanid plasma concentrations [see Clinical Pharmacology (12.3)]. Avoid co-administration of the combination regimen of Pretomanid Tablets, bedaquiline, and linezolid with rifampin, efavirenz, or other strong or moderate CYP3A4 inducers. Refer to the prescribing information for bedaquiline for additional information about drug interactions with CYP3A4.

Lopinavir/Ritonavir

Co-administration of pretomanid with lopinavir/ritonavir did not affect the plasma concentrations of pretomanid [see Clinical Pharmacology (12.3)]. Lopinavir/ritonavir can be co-administered with the combination regimen of Pretomanid Tablets, bedaquiline, and linezolid.

7.2 Effect of Pretomanid on Other Drugs

Midazolam

Co-administration of pretomanid with the CYP3A4 substrate, midazolam, resulted in no clinically significant effect on the pharmacokinetics of midazolam or its major metabolite, 1-hydroxy-midazolam [see Clinical Pharmacology (12.3)]. The combination regimen of Pretomanid Tablets, bedaquiline, and linezolid can be administered with CYP3A4 substrate drugs.

Organic Anion Transporter-3 (OAT3), BCRP, OATP1B3 and P-gp Substrates

The effect of co-administration of pretomanid on the pharmacokinetics of OAT3 substrates in humans is unknown. However, in vitro studies indicate that pretomanid significantly inhibits the OAT3 drug transporter [see Clinical Pharmacology (12.3)], which could result in increased concentrations of OAT3 substrate drugs clinically and may increase the risk of adverse reactions associated with these drugs.

If pretomanid is co-administered with OAT3 substrate drugs (e.g., methotrexate, indomethacin, ciprofloxacin), increase monitoring for OAT3 substrate drug-related adverse reactions and consider dosage reduction for OAT3 substrate drugs, if needed. Refer to the prescribing information of the co-administered drug for dosage reduction information.

In vitro studies cannot exclude the possibility that pretomanid is an inhibitor of BCRP, OATP1B3 and P-gp [see Clinical Pharmacology (12.3)]. No clinical studies have been performed to investigate these interactions. Therefore, it cannot be excluded that co-administration of pretomanid with sensitive OATP1B3 substrates (e.g., valsartan, statins), BCRP substrates (e.g., rosuvastatin, prazosin, glyburide, sulfasalazine) and P-gp substrates (e.g., digoxin, dabigatran etexilate, verapamil) may increase their exposure. If pretomanid is co-administered with substrates of OATP1B3, BCRP, or P-gp, increased monitoring for drug-related adverse reactions to the co-administered medicinal product should be performed.

8 USE IN SPECIFIC POPULATIONS

8.1 Pregnancy

Risk Summary

There are no studies or available data on pretomanid use in pregnant women to inform any drug-associated risks. There are risks associated with active tuberculosis during pregnancy (see Clinical Considerations). When Pretomanid Tablets are administered in combination with bedaquiline and linezolid, the pregnancy information for bedaquiline and linezolid also applies to this combination regimen. Refer to the bedaquiline and linezolid prescribing information for more information on bedaquiline and linezolid associated risks of use during pregnancy. In animal reproduction studies, there was increased post-implantation loss in the presence of maternal toxicity (reduced bodyweight and feed consumption) with oral administration of pretomanid during organogenesis in rats at doses about 4 times the exposure at the recommended dose in humans. There were no adverse embryo fetal effects in rats or rabbits dosed with oral pretomanid during organogenesis at doses up to approximately 2 times the exposure in humans.

The estimated background risk of major birth defects and miscarriage for the indicated population is unknown. All pregnancies have a background risk of birth defect, loss, or other adverse outcomes. In the United States general population, the estimated background risks of major birth defects and miscarriage in clinically recognized pregnancies are 2% to 4% and 15% to 20%, respectively.

Clinical Considerations

Disease-Associated Maternal and/or Embryo/Fetal Risk

Active tuberculosis in pregnancy is associated with adverse maternal and neonatal outcomes including maternal anemia, caesarean delivery, preterm birth, low birth weight, birth asphyxia, and perinatal infant death.

Animal Data

In animal reproduction studies, pregnant rats were dosed orally with pretomanid at 10, 30, and 100 mg/kg/day during organogenesis (gestational Days 7 through 17). Rats showed increased post-implantation loss in the presence of maternal toxicity (including reduced body weight and feed consumption) at 100 mg/kg/day, approximately 4 times the exposure in humans for a 200 mg dose on an AUC basis. There were no adverse embryofetal effects in rats dosed with oral pretomanid during organogenesis at doses up to approximately 2 times the exposure in humans. Pregnant rabbits were dosed orally with pretomanid during organogenesis (gestational Days 7 through 19) at 10, 30, and 60 mg/kg/day. No evidence of adverse developmental outcomes was observed when oral doses of pretomanid were administered to dams during organogenesis (gestational Days 7 to 19) at doses up to 60 mg/kg/day (approximately 2 times the exposure in humans for a 200 mg dose on an AUC basis).

In a pre- and postnatal development study, there were no adverse developmental effects in pups of pregnant rats orally dosed with up to 20 mg/kg/day from gestational Day 6 through lactation Day 20. Pups of pregnant females dosed at 60 mg/kg/day (about 2 times the exposure for the 200 mg dose) had lower body weights and a slight delay in the age at which the air-drop righting reflex developed. These effects occurred at a maternally toxic dose (based on maternal weight loss and reduced food consumption).

8.2 Lactation

Risk Summary

There is no information regarding the presence of pretomanid in human milk, or its effects on milk production or the breastfed infant. Pretomanid was detected in rat milk (see Data). When a drug is present in animal milk, it is likely that the drug will be present in human milk. Because of the potential for adverse reactions in nursing infants, the developmental and health benefits of breastfeeding should be considered along with the mother’s clinical need for Pretomanid Tablets and any potential adverse effects on the breastfed infant from Pretomanid Tablets or from the underlying maternal condition. When Pretomanid Tablets are administered in combination with bedaquiline and linezolid, information on lactation for bedaquiline and linezolid also applies to this combination regimen. Refer to the bedaquiline and linezolid prescribing information for more information on their use during lactation.

Data

Animal Data

In a pre- and postnatal development study in rats treated with pretomanid at doses 0.5 and 2 times the human exposure for a 200 mg dose (AUC) from gestational day 7 through lactation day 20, concentrations in milk on lactation day 14 were 1.4 and 1.6 times higher than the maximum concentration observed in maternal plasma, respectively. The concentration of pretomanid in rat milk does not necessarily predict the concentration of pretomanid in human milk.

8.3 Females and Males of Reproductive Potential

Infertility

Males

Reduced fertility and/or testicular toxicity were observed in male rats and mice treated with oral pretomanid. These effects were associated with hormonal changes including decreased serum inhibin B and increased serum follicle stimulating hormone and luteinizing hormone in rodents [see Nonclinical Toxicology (13.1)].

Reduced fertility and testicular toxicity cannot be definitively ruled out in male human subjects at this time.

8.4 Pediatric Use

Safety and effectiveness of Pretomanid Tablets in pediatric patients have not been established.

8.5 Geriatric Use

Clinical studies of the combination regimen of Pretomanid Tablets, bedaquiline, and linezolid did not include sufficient numbers of subjects aged 65 and over to determine whether they respond differently from younger subjects.

8.6 Hepatic Impairment

The effect of hepatic impairment on the safety, effectiveness, and pharmacokinetics of pretomanid is not known.

8.7 Renal Impairment

The effect of renal impairment on the safety, effectiveness, and pharmacokinetics of pretomanid is not known.

10 OVERDOSAGE

There is no experience with the treatment of acute overdose with pretomanid. Take general measures to support basic vital functions including monitoring of vital signs and ECG (QT interval) in case of deliberate or accidental overdose.

11 DESCRIPTION

Pretomanid is an oral nitroimidazooxazine antimycobacterial drug.

Pretomanid is a white to off-white to yellow-colored powder. The chemical name for pretomanid is (6S)-2-Nitro-6-{[4-(trifluoromethoxy)phenyl]methoxy}-6,7-dihydro-5H-imidazo[2,1-b][1,3]oxazine. The molecular formula for pretomanid is C14H12F3N3O5, and the molecular weight is 359.26. The structural formula of pretomanid is as follows:

Each Pretomanid Tablet contains 200 mg of pretomanid. The inactive ingredients are colloidal silicon dioxide, lactose monohydrate, magnesium stearate, microcrystalline cellulose, povidone, sodium lauryl sulfate, and sodium starch glycolate.

12 CLINICAL PHARMACOLOGY

12.1 Mechanism of Action

Pretomanid is a nitroimidazooxazine antimycobacterial drug [see Microbiology (12.4)].

12.2 Pharmacodynamics

Cardiac Electrophysiology

A randomized, double-blind, placebo- and positive-controlled (moxifloxacin 400 mg), crossover, thorough QT study of pretomanid was performed in 74 healthy adult subjects. At 400 mg (2 times the approved recommended dosage) and 1,000 mg (5 times the approved recommended dosage) single doses of pretomanid, no significant QT prolongation effect was detected.

In Trial 1, patients received the combination regimen of Pretomanid Tablets, bedaquiline, and linezolid for 26 weeks. No patient had QTcF intervals greater than 480 msec, and 1 subject had a post-baseline increase of QTcF of greater than 60 msec following the combination regimen of 200 mg pretomanid once daily, 400 mg bedaquiline once daily for 2 weeks followed by 200 mg bedaquiline 3 times per week thereafter, and 1,200 mg linezolid daily.

In Trial 2, in patients who received the combination regimen of Pretomanid Tablets, bedaquiline, and linezolid for 26 weeks, no patient had QTcF intervals greater than 480 msec or post-baseline increase of QTcF of greater than 60 msec following the combination regimen of 200 mg pretomanid once daily, 200 mg bedaquiline once daily for 8 weeks followed by 100 mg bedaquiline once daily thereafter, and 600 mg or 1,200 mg linezolid daily.

12.3 Pharmacokinetics

Pretomanid AUC and Cmax were approximately dose proportional over a range of single oral doses from 50 mg (0.25 times the approved recommended dosage) to 200 mg (approved recommended dosage); at single doses greater than 200 mg and up to 1,000 mg (5 times the approved recommended dosage), AUC and Cmax increased in a less than dose proportional manner. Steady-state pretomanid plasma concentrations were achieved approximately 4 to 6 days following multiple dose administration of 200 mg, and the accumulation ratio was approximately 2. Pharmacokinetic parameters following single and multiple 200 mg doses of pretomanid in healthy adult subjects are summarized in Table 3.

Table 3: Mean (SD) Pretomanid Pharmacokinetic Parameters in Healthy Adult Subjects Under Fasted and Fed Conditions
PK Parameter | Single Dose 200 mg; Fasted | Single Dose 200 mg; Fed | Steady State 200 mg QD; Fasted
Cmax (µg/mL) | 1.1 (0.2) | 2.0 (0.3) | 1.7 (0.3)
AUCt (µg•hr/mL) | [- AUC96hr] 28.1 (8.0) | 51.6 (10.1) | [- AUC24hr] 30.2 (3.7)
AUCinf (µg•hr/mL) | 28.8 (8.3) | 53.0 (10.6) | ND
[- Median (minimum, maximum)] Tmax (hr) | 4.0 (2.0, 6.0) | 5.0 (3.0, 8.1) | 4.5 (2.0, 8.0)
Vd/F (L) | 180 (51.3) | 97.0 (17.2) | ND
CL/F (L/hr) | 7.6 (2.5) | 3.9 (0.8) | ND
t½ (hr) | 16.9 (3.1) | 17.4 (2.8) | 16.0 (1.6)
ND - Not Determined.

Absorption

Effect of Food

Administration of an oral tablet dose of pretomanid with a high-fat, high-calorie meal (approximately 150, 250, and 500 to 600 calories from protein, carbohydrate, and fat, respectively) increased mean Cmax by 76% and mean AUCinf by 88% as compared with the fasted state (see also Table 3 above).

Distribution

The plasma protein binding of pretomanid is approximately 86.4%.

Elimination

See Table 3 above for estimates of apparent oral clearance and half-life of pretomanid.

Metabolism

Pretomanid is metabolized by multiple reductive and oxidative pathways, with no single pathway considered as major. In vitro studies using recombinant CYP3A4 demonstrated that this enzyme is responsible for up to approximately 20% of the metabolism of pretomanid.

Excretion

In healthy adult males receiving 1,100 mg oral ^14C-radiolabeled pretomanid, a mean (SD) of 53% (3.4%) of a radioactive dose was excreted in urine and 38% (2.7%) in feces, primarily as metabolites; approximately 1% of the radioactive dose was excreted in the urine as unchanged pretomanid.

Specific Populations

No clinically significant differences in the pharmacokinetics of pretomanid were observed based on sex, body weight, race (Black, White, or other), pulmonary TB status (resistant to isoniazid, rifamycins, a fluoroquinolone and a second line injectable antibacterial drug OR resistant to isoniazid and rifampin and treatment intolerant or non-responsive to standard therapy), or HIV status. The effect of renal or hepatic impairment on the pharmacokinetics of pretomanid is unknown.

Drug Interaction Studies

Clinical Studies

Efavirenz: Co-administration of 200 mg QD of pretomanid with efavirenz 600 mg QD for 7 days resulted in a decrease of pretomanid mean AUC by 35% and Cmax by 28%. Mean AUC and Cmax of efavirenz were not affected when given with pretomanid.

Lopinavir/Ritonavir: Co-administration of 200 mg QD pretomanid with lopinavir/ritonavir 400/100 mg BID for 7 days resulted in a decrease of pretomanid mean AUC by 17% and Cmax by 13%. Mean AUC and Cmax of lopinavir were decreased by 14% and 17%, respectively, when given with pretomanid.

Rifampin: Co-administration of 200 mg QD pretomanid with rifampin 600 mg QD for 7 days resulted in a decrease of pretomanid mean AUC by 66% and Cmax by 53%.

Midazolam: Co-administration of 400 mg (twice the approved recommended dosage) QD pretomanid for 14 days and a single 2 mg oral dose of midazolam on Day 14 resulted in a decrease in midazolam mean AUC by 15% and Cmax by 16%, and an increase in 1-hydroxy midazolam mean AUC by 14% and Cmax by 5%.

In Vitro Studies Where Drug Interaction Potential Was Not Further Evaluated Clinically

Cytochrome P450 (CYP) Enzymes: CYP3A4 plays a role in the metabolism of pretomanid, i.e., up to 20%. Pretomanid is not a substrate of CYP2C9, CYP2C19, and CYP2D6. Pretomanid is not an inhibitor of CYP1A2, CYP2C8, CYP2C9, CYP2C19, and CYP2D6 at clinically relevant concentrations based on in vitro studies. Pretomanid is not an inducer of CYP3A4.

Transporter Systems: Pretomanid is an inhibitor of the OAT3 transporter in vitro, which could result in increased concentrations of OAT3 substrate medicinal products clinically and may increase the risk of adverse reactions associated with these medicines. No clinical drug-drug interaction studies have been conducted with OAT3 substrates [see Drug Interactions (7.2)].

In vitro studies cannot exclude the possibility that pretomanid is an inhibitor of BCRP, OATP1B3, and P-gp transporters. The effect of co-administration of pretomanid on the pharmacokinetics of BCRP, OATP1B3 and P-gp substrates in humans is unknown [see Drug Interactions (7.2)].

In vitro studies indicated that pretomanid does not inhibit human OAT1, OCT1, OCT2, OAT1B1, BSEP, MATE1, and/or MATE2-K mediated transport at clinically relevant concentrations of pretomanid. Pretomanid is not a substrate of OAT1, OAT3, OCT2, OAT1B1, OATP1B3, MATE1, MATE2-K, BCRP, and/or P-gp transporters.

12.4 Microbiology

Mechanism of Action

Pretomanid Tablet is a nitroimidazooxazine antimycobacterial drug. Pretomanid kills actively replicating M. tuberculosis by inhibiting mycolic acid biosynthesis, thereby blocking cell wall production. Under anaerobic conditions, against non-replicating bacteria, pretomanid acts as a respiratory poison following nitric oxide release. All of these activities require nitro-reduction of pretomanid within the mycobacterial cell by the deazaflavin-dependent nitroreductase, Ddn, which is dependent on the reduced form of the cofactor F420. Reduction of F420 is accomplished by the F420-dependent glucose-6-phosphate dehydrogenase, Fgd1.

Resistance

Mutations in five M. tuberculosis genes (ddn, fgd1, fbiA, fbiB, and fbiC) have been associated with pretomanid resistance. The products of these genes are involved in bioreductive activation of pretomanid within the bacterial cell. Not all isolates with increased minimum inhibitory concentrations (MICs) have mutations in these genes, suggesting the existence of at least one other mechanism of resistance. The in vitro frequency of resistance development to pretomanid ranged from 10^-7 to 10^-5 at 2 to 6 times the pretomanid MICs. Cross-resistance of pretomanid with other compounds in the same class has been observed.

Antimicrobial Activity

Pretomanid has demonstrated in vitro activity against the M. tuberculosis complex. Pretomanid has also demonstrated anti-M. tuberculosis activity in animal models of tuberculosis [see Indications and Usage (1)].

In murine tuberculosis models, the 3-drug combination of pretomanid, bedaquiline, and linezolid reduced bacterial counts in the lungs to a greater extent and resulted in fewer relapses at 2 and 3 months post-therapy compared to 2-drug combinations of pretomanid, bedaquiline, and linezolid.

In Trial 1, the pretomanid MIC was determined using the Mycobacterial Growth Indicator Tube (MGIT). The baseline pretomanid MIC for M. tuberculosis isolates in the trial ranged from 0.06 to 1 mcg/mL.

In Trial 2, the pretomanid MIC increased from 1 mcg/mL to 16 mcg/mL in seven patients with paired baseline and post 16 weeks isolates. Five patients (two in the linezolid 1,200 mg for 9 weeks arm, three in the linezolid 600 mg for 9 weeks arm) relapsed or failed treatment and one had a favorable outcome. The 9-week dosing regimen is not an approved dosing regimen. Six of the seven patients had elevations in bedaquiline MICs at baseline.

Susceptibility Testing

For specific information regarding susceptibility test criteria and associated test methods and quality control standards recognized by FDA for this drug, please see: https://www.fda.gov/STIC.

13 NONCLINICAL TOXICOLOGY

13.1 Carcinogenesis, Mutagenesis, Impairment of Fertility

Carcinogenesis

No mutagenic or clastogenic effects were detected in conventional genotoxicity studies with pretomanid. A circulating metabolite of pretomanid, M50, was mutagenic in a bacterial reverse mutation assay. No carcinogenic potential was revealed in a 6-month study in transgenic mice where this metabolite was produced. In a 2-year study in rats, there was no evidence of carcinogenic risk.

Mutagenesis

No mutagenic or clastogenic effects were detected in both an in vitro bacterial reverse mutation assay and an in vitro mammalian chromosome aberrations assay using a Chinese hamster ovary cell line. Pretomanid was negative for clastogenicity in a mouse bone marrow micronucleus assay.

A metabolite of pretomanid was mutagenic in a bacterial reverse mutation assay. This metabolite represents approximately 6% of the human exposure (AUC) to pretomanid at the MRHD.

Fertility

In a fertility and general reproduction study in rats, male rats treated orally with pretomanid for 13 to 14 weeks had reduced fertility at 30 mg/kg/day and complete infertility at 100 mg/kg/day (approximately 1 and 2‑times the human exposure for a 200 mg dose, respectively). At 100 mg/kg/day, males had testicular atrophy including hypospermia in the epididymal tubules and focal epithelial hyperplasia of the epididymal tubular epithelium. Following a 10-week treatment-free period, these effects were partially reversed in male rats given pretomanid at 30 mg/kg/day but not at 100 mg/kg/day. These effects were associated with increased serum follicle-stimulating hormone and decreased serum inhibin B concentrations. There were no effects of pretomanid in male rats treated for 13 weeks at 10 mg/kg/day (approximately half of the human exposure for a 200 mg dose). Pretomanid did not affect mating behavior in female rats given oral pretomanid at 100 mg/kg/day for two weeks (approximately twice the human exposure).

Testicular toxicity was present in male mice treated orally for 13 weeks at 20 mg/kg/day [approximately equal to the human exposure (AUC) for a 200 mg dose]. There were no adverse testicular effects observed in mice given pretomanid at 6 mg/kg/day (0.2‑times the human exposure for a 200 mg dose).

Testicular toxicity was observed in male rats following 7 or 14 days of dosing with oral pretomanid at 100 mg/kg/day (approximately 2-times the human exposure for a 200 mg dose). The effects were partially reversible during a 6-month post treatment recovery period in rats treated with pretomanid for 7 days, but not 14 days.

In a 3-month study, decreased sperm motility and total sperm count, and increased abnormal sperm ratio were noted in sexually mature monkeys given ≥150 mg/kg/day (approximately 3 times the human exposure for a 200 mg dose).

13.2 Animal Toxicology and/or Pharmacology

Cataracts were observed in rats treated with pretomanid at doses of 300 mg/kg/day for 13 weeks or 100 mg/kg/day for 26 weeks. There were no cataracts observed in rats given oral pretomanid at 30 mg/kg/day (approximately 2 times the human exposure for a 200 mg dose) for 26 weeks.

In monkeys given oral pretomanid at 450 mg/kg/day for 4 weeks and 300 mg/kg/day for 12 more weeks, cataracts were not present at the end of dosing but developed during the 13‑week post treatment recovery period. In a subsequent study, cataracts were not observed following 13 weeks treatment with up to 300 mg/kg/day oral pretomanid or during the 20-week post treatment recovery period. Further, no cataracts were observed in monkeys given oral pretomanid at 100 mg/kg/day for 39 weeks with a 12-week post treatment recovery. This is approximately 1- to 2-times the human exposure (AUC) for a 200 mg dose.

14 CLINICAL STUDIES

Trial 1

Trial 1 (NCT02333799) was an open-label trial conducted in three centers in South Africa in patients with pulmonary TB resistant to isoniazid, rifamycins, a fluoroquinolone and a second line injectable antibacterial drug (Population 1), or pulmonary TB resistant to isoniazid and rifampin, who were treatment-intolerant or non-responsive to standard therapy (Population 2). Fifty-six (51%) patients were HIV-positive. The patients received a combination regimen of Pretomanid Tablets, bedaquiline, and linezolid for 26 weeks (extended to 9 months in 2 patients) with 24 months of follow-up. The dosage of Pretomanid Tablets was 200 mg orally once daily. The dosage of bedaquiline was 400 mg orally once daily for 2 weeks followed by 200 mg 3 times per week for 24 weeks. The starting dose of linezolid was either 600 mg orally twice daily or 1,200 mg orally once daily. One hundred seven of the 109 patients enrolled were assessable for the primary efficacy analyses with two patients remaining in follow-up for the primary outcome assessment.

Treatment failure was defined as the incidence of bacteriologic failure (reinfection – culture conversion to positive status with a different M. tuberculosis strain), bacteriological relapse (culture conversion to positive status with the same M. tuberculosis strain), or clinical failure (an unfavorable status at, or before, end of treatment (EOT) or failing to attain culture negativity, or if the patient was withdrawn at or before EOT for clinical reasons including retreatment or changing treatment) through follow-up until 6 months after the EOT. Results are presented in Table 4. Of the 107 patients assessed, outcomes were classified as success for 95 (89%) patients and failure for 12 (11%) patients. The success rate significantly exceeded the historical success rates for TB resistant to isoniazid, rifamycins, a fluoroquinolone and a second line injectable antibacterial drug based on a literature review. The outcomes were similar in both HIV negative and HIV positive patients.

Table 4: Outcomes Six Months After the End of Treatment in Population 1 and Population 2 in Trial 1
Outcome |  | Total | Population 1 [Population 1 = TB resistant to isoniazid, rifamycins, a fluoroquinolone and a second line injectable antibacterial drug;] | Population 2 [Population 2 = TB resistant to isoniazid and rifampin, who were treatment-intolerant or nonresponsive to standard therapy]
Outcome | Total assessable | 107 | 71 | 36
Success | Success (culture negative status at 6 months post treatment) | 95 (89%) | 63 (89%) | 32 (89%)
Failure | Death | 7 | 6 | 1
Failure | Relapse post treatment | 2 | 1 [The patient died at Day 486.] | 1
Failure | Withdrawal, loss to follow-up, or contaminated cultures | 3 | 1 | 2
 | Total Failure | 12 (11%) | 8 (11%) | 4 (11%)

Trial 2

Trial 2 (NCT03086486) was a phase 3 partially blinded, randomized trial assessing the safety and efficacy of various doses and treatment durations of linezolid plus Pretomanid Tablets and bedaquiline in patients with pulmonary TB resistant to isoniazid, rifamycins, a fluoroquinolone and a second line injectable antibacterial drug, or pulmonary TB resistant to rifamycins and either a fluoroquinolone or a second line injectable antibacterial drug, or pulmonary TB resistant to isoniazid and rifampin who were treatment intolerant or non-responsive to standard therapy.

A total of 181 patients were randomized to receive one of 4 treatment regimens, of which 45 each received 1,200 mg or 600 mg linezolid orally plus Pretomanid Tablets and bedaquiline for 26 weeks, and 46 and 45 patients received 1,200 mg or 600 mg linezolid orally for 9 weeks (not an approved dosing regimen), followed by linezolid placebo for 17 weeks, respectively, plus Pretomanid Tablets and bedaquiline for 26 weeks. The dosage of Pretomanid Tablets was 200 mg orally once daily for 26 weeks. The dosage of bedaquiline was 200 mg daily for 8 weeks, followed by 100 mg daily for 18 weeks.

Treatment failure was defined as the incidence of bacteriologic failure, bacteriologic relapse or clinical failure through follow-up until 6 months after the end of treatment, which was identical to the definition of treatment failure in Trial 1.

The success rate in each treatment arm significantly exceeded the historical success rates for TB resistant to isoniazid, rifamycins, a fluoroquinolone and a second line injectable antibacterial drug based on a literature review used in Trial 1. When used in combination with Pretomanid Tablets and bedaquiline, linezolid 600 mg once daily for 26 weeks is preferred over linezolid 1,200 mg once daily for 26 weeks [see Dosage and Administration (2.2)].

Among the 90 patients receiving linezolid for 26 weeks, the mean age of the patients was 38 years old with 68% being males. Most patients were White (64%), and the remaining patients were Black (36%). Most patients had a current diagnosis (a stratification factor) of pulmonary TB resistant to rifamycins and either a fluoroquinolone or a second line injectable antibacterial drug (46%) or pulmonary TB resistant to isoniazid, rifamycins, a fluoroquinolone and a second line injectable antibacterial drug (44%), and the remainder were patients having pulmonary TB resistant to isoniazid and rifampin who were treatment intolerant or non-responsive to standard therapy (6% and 4%, respectively). The results are presented in Table 5 below.

Table 5: Outcomes Six Months After the End of Treatment [Linezolid was administered with Pretomanid Tablets and bedaquiline.] for All Randomized Patients [The primary efficacy analysis excluded one randomized subject who was lost to follow-up after repeated negative cultures during the follow-up period.] [Refers to patients with pulmonary TB resistant to isoniazid, rifamycins, a fluoroquinolone and a second line injectable antibacterial drug or patients with pulmonary TB resistant to isoniazid and rifampin, and who are treatment-intolerant or nonresponsive to standard therapy.] in 26-Week Regimens in Trial 2:
Outcome |  | Linezolid 1,200 mg [When used in combination with Pretomanid Tablets and bedaquiline, linezolid 600 mg once daily for 26 weeks is preferred over linezolid 1,200 mg once daily for 26 weeks based on safety profiles [see Dosage and Administration (2.2) and Adverse Reactions (6.1)].]; 26 weeks; (N = 44); n (%) | Linezolid; 600 mg; 26 weeks; (N = 45); n (%)
Success |  | 41 (93%) | 41 (91%)
Failure | Relapse post treatment | 0 | 1 (2%)
Failure | Re-treated post treatment | 2 (5%) | 1 (2%)
Failure | Loss to follow-up or withdrawal | 1 (2%) | 2 (4%)
 | Total Failure | 3 (7%) | 4 (9%)
N = total number of patients in the relevant analysis population; n = number of patients in each category.

16 HOW SUPPLIED/STORAGE AND HANDLING

Pretomanid Tablet 200 mg is packaged in either white, round, high-density polyethylene bottles with polypropylene child-resistant closure or child-resistant blister packages comprised of a polyvinylchloride film with foil and paper backing.

Pretomanid Tablet 200 mg is a white to off-white, oval tablet debossed with M on one side and P200 on the other side.

NDC Number | Size
49502-476-26 | Bottle of 26
49502-476-14 | Unit dose blister pack of 14 (1 strip of 14 tablets)
49502-476-29 | Unit dose blister pack of 100 (10 strips of 10 tablets)
49502-476-72 | Bottle of 182

Store below 30°C (86°F).

Dispense only in original container and keep container tightly closed.

17 PATIENT COUNSELING INFORMATION

Advise the patient to read the FDA-approved patient labeling (Medication Guide).

Important Information on Co-administration of Pretomanid Tablets in Combination with Bedaquiline and Linezolid [see Dosage and Administration (2.1)]

- Inform the patient or caregiver that Pretomanid Tablets administered as a combination regimen with bedaquiline and linezolid would be useful only in adult patients with TB resistant to isoniazid, rifamycins, a fluoroquinolone and a second line injectable antibacterial drug or TB resistant to isoniazid and rifampin, who are treatment-intolerant or nonresponsive to standard therapy. This regimen is not indicated for treatment in patients with latent infection or extra-pulmonary infection due to M. tuberculosis, drug-sensitive TB, TB resistant to isoniazid and rifampin who are responsive to standard therapy and not treatment-intolerant, or who have TB with known resistance to any component of the regimen (Pretomanid Tablets, bedaquiline, or linezolid).
- Instruct the patient or caregiver that the combination regimen of Pretomanid Tablets, bedaquiline, and linezolid must be administered by directly observed therapy (DOT).
- Inform patients of safety concerns associated with linezolid and bedaquiline and advise the patient or their caregiver to read the Medication Guide for bedaquiline.

Serious Adverse Reactions

Advise patients that the following serious adverse reactions can occur with the combination regimen of Pretomanid Tablets, bedaquiline, and linezolid: liver enzyme abnormalities, myelosuppression including anemia, peripheral and optic neuropathy, and cardiac rhythm abnormalities [see Warnings and Precautions (5.2, 5.4)].

Additional serious adverse reactions can occur with the use of linezolid, including serotonin syndrome, lactic acidosis, and convulsions. Refer to the prescribing information for linezolid for additional counseling information for these serious adverse reactions.

Peripheral and Optic Neuropathy

Advise patients to promptly inform their physician if they experience changes in vision during linezolid therapy. Monitor visual function in all patients receiving linezolid. Counsel patients to obtain prompt ophthalmological evaluation if the patient experiences symptoms of visual impairment [see Warnings and Precautions (5.3)].

Interruption of Linezolid Dosing to Manage Linezolid Adverse Reactions

Counsel patients that linezolid dosing may be modified or interrupted during the therapy to manage the known linezolid adverse reactions of myelosuppression, peripheral neuropathy, and optic neuropathy [see Dosage and Administration section (2.2) and Adverse Reactions (6)].

Compliance with Treatment

Inform patients that Pretomanid Tablets must be taken as part of a combination regimen with bedaquiline and linezolid. Compliance with the full course of therapy must be emphasized. Advise patients that although it is common to feel better early in the course of therapy, the medication should be taken exactly as directed for the full prescribed duration of dosing. Skipping doses other than as directed by a physician or not completing the full course of therapy may (1) decrease the effectiveness of the immediate treatment and (2) increase the likelihood that their Mycobacterium may develop resistance and the disease will not be treatable by the regimen or other antibacterial drugs in the future.

Important Administration Instructions

- Inform patients to take the regimen with food. Doses of the combination regimen of Pretomanid Tablets, bedaquiline, and linezolid missed for safety reasons can be made up at the end of treatment; doses of linezolid alone missed due to linezolid adverse reactions should not be made up. If bedaquiline and/or Pretomanid Tablets are permanently discontinued, the entire combination regimen of Pretomanid Tablets, bedaquiline, and linezolid should be discontinued.
- Advise patients who have difficulty swallowing tablets that Pretomanid Tablets can be crushed and suspended in water at room temperature. Alternately, the tablet can be soaked for 4 to 5 minutes in room temperature water and then the remaining solid crushed [see Dosage and Administration (2.2)].

Use in Patients with Hepatic or Renal Impairment

Advise patients to inform their physician if they have a history of liver or kidney problems. The safety and effectiveness of the combination regimen of Pretomanid Tablets, bedaquiline, and linezolid in populations with hepatic or renal impairment have not been established.

Use with Alcohol and Other Medications

Advise patients to discuss with their physician the other medications they are taking and other medical conditions before starting treatment with Pretomanid Tablets.

Advise patients to abstain from alcohol, hepatotoxic medications, and herbal products [see Drug Interactions (7)].

Manufactured by:
Mylan Laboratories Limited
Hyderabad, 500 096, India

Manufactured for:
Mylan Specialty L.P.
Morgantown, WV 26505 U.S.A.
Under license from TB Alliance.

MS:MXA:PRET:R4

MEDICATION GUIDE

Pretomanid Tablets (Pre-TOH-mah-nid) Limited Population

What is the most important information I should know about the combination regimen of Pretomanid Tablets, bedaquiline, and linezolid?

Pretomanid Tablets are for use only as part of a combination antibiotic regimen that includes Pretomanid Tablets, bedaquiline, and linezolid.

Treatment with the combination regimen of Pretomanid Tablets, bedaquiline, and linezolid can cause serious side effects. See “What are the possible side effects of the combination regimen of Pretomanid Tablets, bedaquiline, and linezolid?”

Read the Medication Guide that comes with bedaquiline. Ask your healthcare provider for information about linezolid. The serious side effects that can happen when taking bedaquiline and linezolid can also happen when taken in the combination regimen of Pretomanid Tablets, bedaquiline, and linezolid.

What is the combination regimen of Pretomanid Tablets, bedaquiline, and linezolid?

Pretomanid Tablets are a prescription medicine used as part of a combination regimen with bedaquiline and linezolid. The combination regimen of Pretomanid Tablets, bedaquiline, and linezolid includes three prescription antibiotics that are used together in adults to treat tuberculosis (TB) of the lungs that is resistant to other classes of antibiotics (isoniazid, rifamycins, a fluoroquinolone and a second line injectable antibiotic) or in adults who cannot tolerate or do not respond to treatment for TB that is resistant to two specific antibiotics (isoniazid and rifampin).

Pretomanid Tablets are not for use in people who have:

- TB that is not resistant to antibiotics.
- an inactive (latent) TB infection.
- a type of TB other than TB of the lungs.
- TB resistant to isoniazid and rifampin who can tolerate or who respond to medicines usually used to treat this type of TB.
- TB that is known to be resistant to Pretomanid Tablets, bedaquiline, or linezolid.

It is not known if Pretomanid Tablets are safe and effective for use except in combination with bedaquiline and linezolid as part of the recommended dosing regimen.

It is not known if Pretomanid Tablets are safe and effective in children.

Pretomanid Tablets were approved by FDA using the Limited Population pathway. This means FDA has approved this drug for a limited and specific patient population, and studies on the drug may have only answered focused questions about its safety and effectiveness.

Do not take the combination regimen of Pretomanid Tablets, bedaquiline, and linezolid if:

- you have been told by your healthcare provider not to take bedaquiline or linezolid.

Before you take the combination regimen of Pretomanid Tablets, bedaquiline, and linezolid, tell your healthcare provider about all of your medical conditions, including if you:

- have liver problems. See “What are the possible side effects of the combination regimen of Pretomanid Tablets, bedaquiline, and linezolid?”
- have kidney problems.
- have or have had an abnormal heart rhythm (ECG) or other heart problems, including heart failure.
- have a family history of a heart problem called “congenital long QT syndrome.”
- have decreased thyroid gland function (hypothyroidism).
- have HIV infection.
- have been told that you have low levels of calcium, magnesium or potassium in your blood.
- have ever had a seizure.
- are pregnant or plan to become pregnant. It is not known if pretomanid will harm your unborn baby. Talk to your healthcare provider about the possible risks to your baby if you take the combination regimen of Pretomanid Tablets, bedaquiline, and linezolid while you are pregnant.
- are breastfeeding or plan to breastfeed. It is not known if pretomanid passes into your breast milk. Talk to your healthcare provider about the best way to feed your baby if you take the combination regimen of Pretomanid Tablets, bedaquiline, and linezolid.

Tell your healthcare provider about all the medicines you take, including prescription and over-the-counter medicines, vitamins, and herbal supplements. You should not take herbal products or medicines that can harm your liver during treatment with the combination regimen of Pretomanid Tablets, bedaquiline, and linezolid.

The combination regimen of Pretomanid Tablets, bedaquiline, and linezolid regimen may affect how other medicines work, and other medicines may affect how the combination regimen of Pretomanid Tablets, bedaquiline, and linezolid works.

Especially tell your healthcare provider if you take:

- a type of medicine called a CYP3A4 inducer, such as efavirenz or rifampin. Ask your healthcare provider if you are not sure.

How should I take the combination regimen of Pretomanid Tablets, bedaquiline and linezolid?

- Pretomanid Tablets must only be taken with bedaquiline and linezolid as part of the dosing regimen prescribed by your healthcare provider.
- Take the combination regimen of Pretomanid Tablets, bedaquiline, and linezolid exactly as your healthcare provider tells you to take it.
- It is important that you complete the full course of treatment with the combination regimen of Pretomanid Tablets, bedaquiline, and linezolid, and not miss any doses, even if you feel better before you have completed the full course of treatment. Missing doses may decrease the effectiveness of the treatment and increase the chance that your TB will not be treatable by the combination regimen of Pretomanid Tablets, bedaquiline, and linezolid or other medicines.
- Take the combination regimen of Pretomanid Tablets, bedaquiline, and linezolid for a total of 26 weeks.
  - Your healthcare provider will tell you if you should take the combination regimen of Pretomanid Tablets, bedaquiline, and linezolid for longer than 26 weeks.
  - Your healthcare provider will tell you if you should stop taking linezolid before you have taken it for 26 weeks or if you should reduce your dose of linezolid due to side effects.
- Your healthcare provider or caregiver will watch you take your doses of Pretomanid Tablets, bedaquiline, and linezolid.
- Take Pretomanid Tablets, bedaquiline, and linezolid with food.
  - If you can swallow whole tablets:
    - Swallow tablets whole with water.
  - If you cannot swallow whole tablets:
    - Crush 200 mg of Pretomanid Tablets (1 tablet) and mix with 1 teaspoon (5 mL) of room temperature drinking water. Mix well in a drinking cup.
    - Swallow mixture immediately.
    - Make sure no remaining medicine is left in the drinking cup. Rinse well with another 1 teaspoon (5 mL) of room temperature drinking water and swallow the mixture immediately.
    - Do not store mixture for later use. Or
    - Soak 200 mg of Pretomanid Tablets (1 tablet) in 1 teaspoon (5 mL) of room temperature drinking water for 4 to 5 minutes in a drinking cup. Then crush the tablet in the drinking cup. Mix the medicine in the drinking cup well by stirring.
    - Swallow the mixture immediately.
    - Make sure no remaining medicine is left in the drinking cup. Rinse well with another 1 teaspoon (5 mL) of room temperature drinking water and swallow the mixture immediately.
    - Do not store the mixture for later use.
- Week 1 and Week 2:
  - Take 200 mg of Pretomanid Tablets (1 tablet), 400 mg of bedaquiline, and 600 mg of linezolid 1 time each day. Or
  - Take 200 mg of Pretomanid Tablets (1 tablet), 400 mg of bedaquiline, and 1,200 mg of linezolid 1 time each day.
- Week 3 to Week 26:
  - Take 200 mg of Pretomanid Tablets (1 tablet) and 600 mg of linezolid 1 time each day. Or
  - Take 200 mg of Pretomanid Tablets (1 tablet) and 1,200 mg of linezolid 1 time each day.
  - Take 200 mg of bedaquiline 3 times a week.
    - Take your doses of bedaquiline at least 48 hours apart. For example, you may take bedaquiline on Monday, Wednesday, and Friday every week from Week 3 to Week 26. Or
- Week 1 to Week 8:
  - Take 200 mg of bedaquiline 1 time each day for 8 weeks. Then take 100 mg of bedaquiline 1 time each day for 18 weeks, for a total of 26 weeks.
- You may need to take the combination regimen of Pretomanid Tablets, bedaquiline, and linezolid for longer than 26 weeks. Talk with your healthcare provider.
- Do not miss a dose of Pretomanid Tablets, bedaquiline, or linezolid unless instructed to do so by your healthcare provider. If you miss doses or do not complete the total 26 weeks of treatment, your treatment may not work as well, and your TB may be harder to treat.
- If your healthcare provider tells you to stop taking the combination regimen of Pretomanid Tablets, bedaquiline, and linezolid for a period of time, follow the instructions given to you by your healthcare provider for taking the missed doses at the end of your treatment. You should not make up any missed doses of linezolid alone that your healthcare provider told you not to take due to side effects.
- If you miss a dose of Pretomanid Tablets, bedaquiline, or linezolid and you are not sure what to do, talk to your healthcare provider as soon as possible.
- If you take too much Pretomanid Tablets, go to the nearest hospital emergency room right away.

Do not stop taking Pretomanid Tablets, bedaquiline, or linezolid without first talking to your healthcare provider.

What should I avoid when taking the combination regimen of Pretomanid Tablets, bedaquiline, and linezolid?

- You should not drink alcohol while taking the combination regimen of Pretomanid Tablets, bedaquiline, and linezolid.

What are the possible side effects of the combination regimen of Pretomanid Tablets, bedaquiline, and linezolid?

The combination regimen of Pretomanid Tablets, bedaquiline, and linezolid may cause serious side effects including:

- See “What is the most important information I should know about the combination regimen of Pretomanid Tablets, bedaquiline, and linezolid?”
- Liver problems. Your healthcare provider should do blood tests to check your liver at least before you start taking the combination regimen of Pretomanid Tablets, bedaquiline, and linezolid, 2 weeks after starting treatment, and then monthly during treatment. Tell your healthcare provider right away if you have symptoms of liver problems, such as:

- unusual tiredness
- loss of appetite
- nausea
- yellowing of your skin or the whites of your eyes

- dark (tea-colored) urine
- tenderness in the upper right side of your stomach-area (abdomen)

See “What should I avoid when taking the combination regimen of Pretomanid Tablets, bedaquiline, and linezolid?”
2. Low blood cell counts. The combination regimen of Pretomanid Tablets, bedaquiline, and linezolid can cause low red blood cell counts (anemia), low white blood cell counts (leukopenia), low blood platelet counts (thrombocytopenia) or a combination of low red and white blood cell counts and low blood platelet counts (pancytopenia). Low blood cell counts are a side effect of linezolid. Anemia is a common side effect of linezolid, but can be serious and life-threatening. Low blood cell counts were reversible when linezolid treatment was reduced, stopped for a period of time, or stopped permanently. Your healthcare provider should check your blood cell counts at least before you start taking the combination regimen of Pretomanid Tablets, bedaquiline, and linezolid, 2 weeks after starting treatment, and then monthly during treatment. Your healthcare provider may lower the dose or stop treatment with linezolid if you develop or have worsening blood cell counts.
3. Nerve problems in your arms, hands, legs, and feet (peripheral neuropathy). The combination regimen of Pretomanid Tablets, bedaquiline, and linezolid can cause nerve problems in your arms, hands, legs, and feet. Tell your healthcare provider if you have symptoms of nerve problems in your arms, hands, legs, or feet, including:

  - numbness
  - burning
  - a feeling of “pins and needles”

2. tremors
3. problems with balance
4. weakness

- Vision problems. The combination regimen of Pretomanid Tablets, bedaquiline, and linezolid can cause nerve problems in your eyes (optic neuropathy). Nerve problems in your eyes can cause problems with your vision. Tell your healthcare provider right away if you have symptoms of nerve problems in your eyes, such as changes in vision.
Nerve problems in your arms, hands, legs, feet, and eyes are common side effects of long-term use of linezolid, but can be serious. Nerve problems caused by linezolid were generally reversible or improved when symptoms of nerve problems were monitored by the healthcare provider and linezolid treatment was reduced, stopped for a period of time, or stopped permanently.
- Heart rhythm problem called QT prolongation. The combination regimen of Pretomanid Tablets, bedaquiline, and linezolid can cause a heart rhythm problem. Heart rhythm problem is a side effect of bedaquiline. Your healthcare provider should do a test called an electrocardiogram (ECG) to check your heart before you start taking the combination regimen of Pretomanid Tablets, bedaquiline, and linezolid and at least 2, 12, and 24 weeks after starting treatment. Tell your healthcare provider right away if you:

  - have a change in heartbeat (a fast or irregular heartbeat)

- feel dizzy or faint

- Effects on male fertility. It is not known if pretomanid can cause fertility problems in males. This could affect your ability to father a child. Talk to your healthcare provider if this is a concern for you.
- Build-up of an acid in your blood (lactic acidosis). The combination regimen of Pretomanid Tablets, bedaquiline, and linezolid can cause a build-up of acid in your blood. A build-up of acid in your blood is a side effect of linezolid.
- Call your healthcare provider right away if you have nausea and vomiting that keep coming back.

The most common side effects of the combination regimen of Pretomanid Tablets, bedaquiline, and linezolid include:

- nausea
- acne
- vomiting
- abnormal blood tests that may be due to injury to your liver
- headache
- muscle and bone pain
- heartburn

- rash
- itching
- decreased appetite
- stomach area (abdominal) pain
- chest pain that worsens when you breathe or cough
- coughing up blood

- abnormal blood tests that may be due to injury to your pancreas

These are not all the possible side effects of the combination regimen of Pretomanid Tablets, bedaquiline, and linezolid. For more information, ask your healthcare provider or pharmacist.

Call your doctor for medical advice about side effects. You may report side effects to FDA at 1-800-FDA-1088.

How should I store Pretomanid Tablets?

- Store Pretomanid Tablets, bedaquiline, and linezolid below 86°F (30°C). Ask your pharmacist if you have questions about how to store bedaquiline and linezolid.
- Keep Pretomanid Tablets in the original container with the container tightly closed.

Keep Pretomanid Tablets and all medicines out of the reach of children.

General information about the safe and effective use of the combination regimen of Pretomanid Tablets, bedaquiline, and linezolid.

Medicines are sometimes prescribed for purposes other than those listed in a Medication Guide. Do not use Pretomanid Tablets, bedaquiline, or linezolid for a condition for which it was not prescribed. Do not give Pretomanid Tablets, bedaquiline, or linezolid to other people, even if they have the same symptoms that you have. This may harm them. You can ask your pharmacist or healthcare provider for information about Pretomanid Tablets, bedaquiline, and linezolid that is written for health professionals.

What are the ingredients in the combination regimen of Pretomanid Tablets, bedaquiline, and linezolid?

Pretomanid Tablets active ingredient: pretomanid

Pretomanid Tablets inactive ingredients: colloidal silicon dioxide, lactose monohydrate, magnesium stearate, microcrystalline cellulose, povidone, sodium lauryl sulfate, and sodium starch glycolate

The ingredients for bedaquiline can be found in the Medication Guide for bedaquiline. The ingredients for linezolid can be found in the information about linezolid that is written for health professionals.

Manufactured by:
Mylan Laboratories Limited
Hyderabad, 500 096, India

Manufactured for:
Mylan Specialty L.P.
Morgantown, WV 26505 U.S.A.
Under license from TB Alliance.

For more information, call Mylan at 1-877-446-3679 (1-877-4-INFO-RX).

MS:MXA:MG:PRET:R4

This Medication Guide has been approved by the U.S. Food and Drug Administration.

Revised: 11/2024

PRINCIPAL DISPLAY PANEL – 200 mg

NDC 49502-476-26

Rx only

Pretomanid
Tablets

200 mg

Limited
Population*

Dispense the enclosed
Medication Guide to
each patient.

*See the full prescribing
information for Pretomanid
Tablets 200 mg for information
about the limited population.

26 tablets

Each tablet contains:
Pretomanid 200 mg

Recommended Dosage:
see Prescribing Information.

Keep this and all medication
out of the reach of children.

Store below 30°C (86°F).

Dispense only in original container.

Keep container tightly closed.

Manufactured by: Mylan Laboratories Limited
Hyderabad - 500 096, India

Manufactured for: Mylan Specialty L.P.
Morgantown, WV 26505 U.S.A.

Under license from TB Alliance.

Code No.: MH/DRUGS/AD/089

MS:MXA:47626:1C:R3

Mylan.com